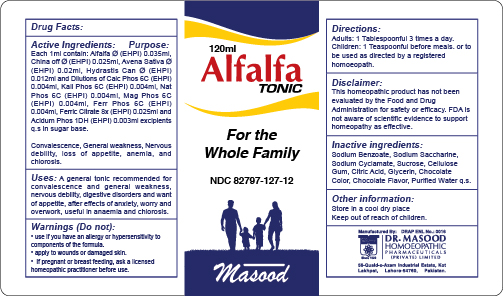 DRUG LABEL: Alfalfa Tonic
NDC: 82797-127 | Form: SYRUP
Manufacturer: Dr. Masood Homeopathic Pharmaceuticals Private Limited
Category: homeopathic | Type: HUMAN OTC DRUG LABEL
Date: 20240516

ACTIVE INGREDIENTS: AVENA SATIVA WHOLE 2.4 mg/120 mL; HYDRASTIS CANADENSIS WHOLE 1.44 mg/120 mL; DIBASIC POTASSIUM PHOSPHATE 0.48 mg/120 mL; SODIUM PHOSPHATE 0.48 mg/120 mL; ALFALFA 4.2 mg/120 mL; MAGNESIUM PHOSPHATE, DIBASIC 0.48 mg/120 mL; FERROUS PHOSPHATE 0.48 mg/120 mL; FERRIC CITRATE ANHYDROUS 3 mg/120 mL; CINCHONA BARK 3 mg/120 mL; CALCIUM PHOSPHATE 0.48 mg/120 mL; PHOSPHORIC ACID 0.36 mg/120 mL
INACTIVE INGREDIENTS: CARBOXYMETHYLCELLULOSE SODIUM 5.1 mg/120 mL; SODIUM BENZOATE 0.75 mg/120 mL; ANHYDROUS CITRIC ACID 0.425 mg/120 mL; GLYCERIN 30 mL/120 mL; WATER 120 mL/120 mL; SODIUM CYCLAMATE 375.6 mg/120 mL; SUCROSE 600 mg/120 mL

Dosage and Administration:

Adults: 1 tablespoonful 3 times a day before meal.

Children: 1 teaspoonful before meal.

Or to be used as directed by registered Homeopathic physician

Indications and Usage :

Convalescence, General weakness, Nervous debility, loss of appetite, anemia, and chlorosis.

Active Ingredients:

Alfalfa

China off

Avena Sativa

Hydrastis Can

Calc Phos

Kali Phos

Nat Phos

Mag Phos

Ferr Phos

Ferric Citrate

Acidum Phos

Keep out of reach of children:

Keep this and all medicnes out of reach of children

Purpose:

ALFALFA: Improves appetite and helps in digestion resulting in improved mental and physical health and weight gain. Improves lactation in nursing women.

AVENA SATIVA: for debility after exhausting diseases. Has a selective action on the brain and nervous system, favorably influencing their nutritive function.

CHINA OFF: Helps against exhaustion from general debility.

HYDRASTIS CAN: Ideal for muscular power, also increases appetite.

CALC PHOS: for bone development and anemia after acute and chronic wasting diseases.

KALI PHOS: Helps in weakness and fatigue.

NATPHOS: Strengthens muscles & bones.

MAG PHOS: Helps in relieving muscular cramps.

FERR PHOS: Remedy for the first stage of all febrile conditions.

FERRIC AMMONIUM CITRATE: It compensates for the generalized weakness of the body due to anemia.

Warnings:

Do not:

- use if you have an allergy or hypersensitivity to components of the formula
- use if pregnant or nursing

Stop use and ask a doctor if:

- condition worsens
- If symptoms persists for more than 7 days

Inactive Ingredients:

Sodium Benzoate

Sodium Saccharine

Sodium Cyclamate

Sucrose

Cellulose Gum

Citric acid

Glycerin